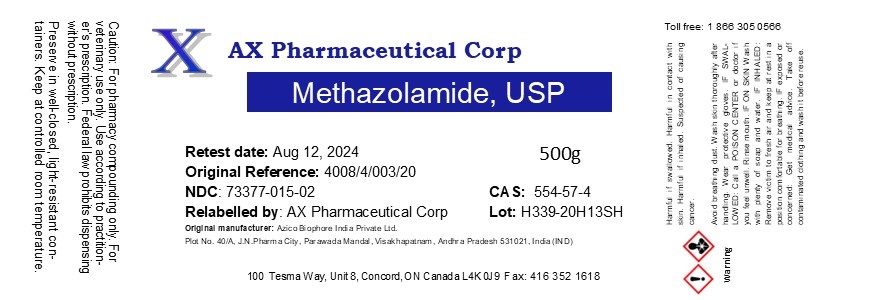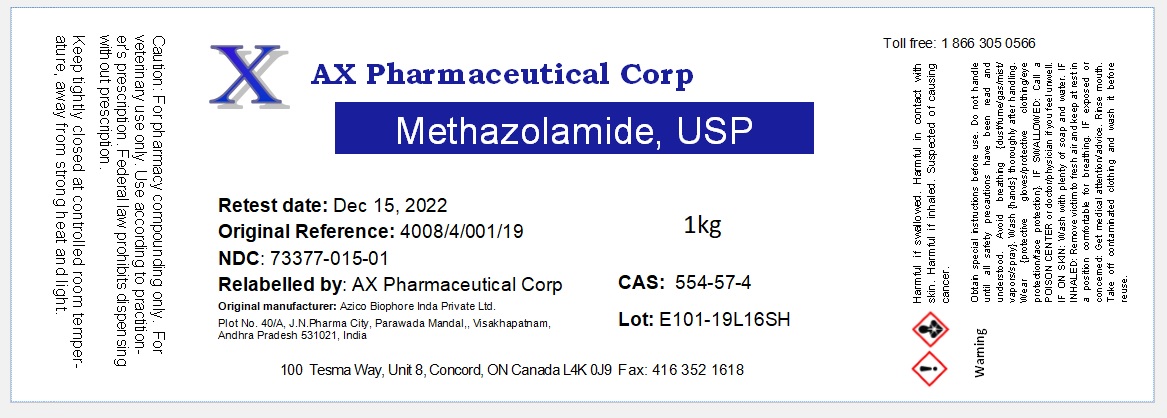 DRUG LABEL: Methazolamide
NDC: 73377-015 | Form: POWDER
Manufacturer: AX Pharmaceutical Corp
Category: other | Type: BULK INGREDIENT - ANIMAL DRUG
Date: 20220831

ACTIVE INGREDIENTS: Methazolamide 1 kg/1 kg

Methazolamide